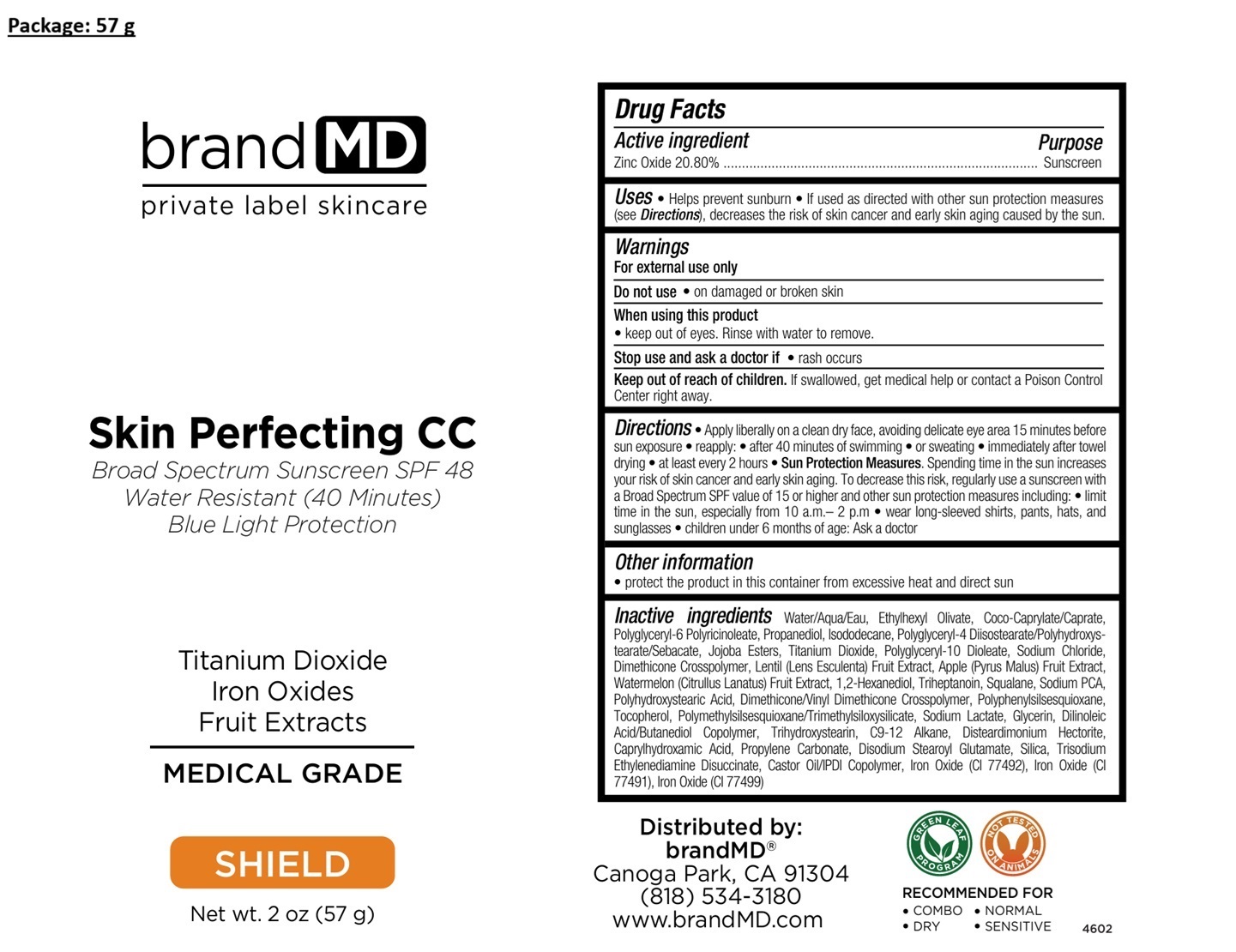 DRUG LABEL: Skin Perfecting CC Broad Spectrum Sunscreen SPF 48
NDC: 72957-014 | Form: CREAM
Manufacturer: Private Label Skin Care
Category: otc | Type: HUMAN OTC DRUG LABEL
Date: 20260108

ACTIVE INGREDIENTS: ZINC OXIDE 20.80 g/100 g
INACTIVE INGREDIENTS: WATER; ETHYLHEXYL OLIVATE; COCOYL CAPRYLOCAPRATE; POLYGLYCERYL-6 POLYRICINOLEATE; PROPANEDIOL; ISODODECANE; POLYGLYCERYL-4 DIISOSTEARATE/POLYHYDROXYSTEARATE/SEBACATE; HYDROGENATED JOJOBA OIL, RANDOMIZED; TITANIUM DIOXIDE; POLYGLYCERYL-10 DIOLEATE; SODIUM CHLORIDE; DIMETHICONE CROSSPOLYMER (180000 MPA.S); VICIA LENS FRUIT; APPLE; WATERMELON; 1,2-HEXANEDIOL; TRIHEPTANOIN; SQUALANE; SODIUM PYRROLIDONE CARBOXYLATE; POLYHYDROXYSTEARIC ACID (2300 MW); DIMETHICONE/VINYL DIMETHICONE CROSSPOLYMER (SOFT PARTICLE); PHENYLSILANETRIOL; TOCOPHEROL; POLYMETHYLSILSESQUIOXANE/TRIMETHYLSILOXYSILICATE; SODIUM LACTATE; GLYCERIN; DILINOLEIC ACID/BUTANEDIOL COPOLYMER; TRIHYDROXYSTEARIN; C9-12 ALKANE; DISTEARDIMONIUM HECTORITE; CAPRYLHYDROXAMIC ACID; PROPYLENE CARBONATE; DISODIUM STEAROYL GLUTAMATE; SILICON DIOXIDE; TRISODIUM ETHYLENEDIAMINE DISUCCINATE; CASTOR OIL/IPDI COPOLYMER; FERRIC OXIDE YELLOW; FERRIC OXIDE RED; FERROSOFERRIC OXIDE

Skin Perfecting CC Broad Spectrum Sunscreen SPF 48

Active ingredient

Zinc Oxide 20.80%

Purpose

Sunscreen

Uses

• Helps prevent sunburn • If used as directed with other sun protection measures (see Directions), decreases the risk of skin cancer and early skin aging caused by the sun.

Warnings

For external use only

Do not use • on damaged or broken skin

When using this product
• keep out of eyes. Rinse with water to remove.

Stop use and ask a doctor if • rash occurs

Keep out of reach of children. If swallowed, get medical help or contact a Poison Control Center right away.

Directions

• Apply liberally on a clean dry face, avoiding delicate eye area 15 minutes before sun exposure • reapply: • after 40 minutes of swimming • or sweating • immediately after towel drying • at least every 2 hours • Sun Protection Measures. Spending time in the sun increases your risk of skin cancer and early skin aging. To decrease this risk, regularly use a sunscreen with a Broad Spectrum SPF value of 15 or higher and other sun protection measures including: • limit time in the sun, especially from 10 a.m.– 2 p.m • wear long-sleeved shirts, pants, hats, and sunglasses • children under 6 months of age: Ask a doctor

Other information

• protect the product in this container from excessive heat and direct sun

Inactive ingredients

Water/Aqua/Eau, Ethylhexyl Olivate, Coco-Caprylate/Caprate, Polyglyceryl-6 Polyricinoleate, Propanediol, Isododecane, Polyglyceryl-4 Diisostearate/Polyhydroxystearate/Sebacate, Jojoba Esters, Titanium Dioxide, Polyglyceryl-10 Dioleate, Sodium Chloride, Dimethicone Crosspolymer, Lentil (Lens Esculenta) Fruit Extract, Apple (Pyrus Malus) Fruit Extract, Watermelon (Citrullus Lanatus) Fruit Extract, 1,2-Hexanediol, Triheptanoin, Squalane, Sodium PCA, Polyhydroxystearic Acid, Dimethicone/Vinyl Dimethicone Crosspolymer, Polyphenylsilsesquioxane, Tocopherol, Polymethylsilsesquioxane/Trimethylsiloxysilicate, Sodium Lactate, Glycerin, Dilinoleic Acid/Butanediol Copolymer, Trihydroxystearin, C9-12 Alkane, Disteardimonium Hectorite, Caprylhydroxamic Acid, Propylene Carbonate, Disodium Stearoyl Glutamate, Silica, Trisodium Ethylenediamine Disuccinate, Castor Oil/IPDI Copolymer, Iron Oxide (CI 77492), Iron Oxide (CI 77491), Iron Oxide (CI 77499)

brand MD

Water Resistant (40 Minutes)
Blue Light Protection

Titanium Dioxide
Iron Oxides
Fruit Extracts

MEDICAL GRADE

SHIELD

Distributed by:
brandMD®
Canoga Park, CA 91304
(818) 534-3180
www.brandMD.com

GREEN LEAF PROGRAM

NOT TESTED ON ANIMALS

RECOMMENDED FOR
• COMBO
• DRY
• NORMAL
• SENSITIVE